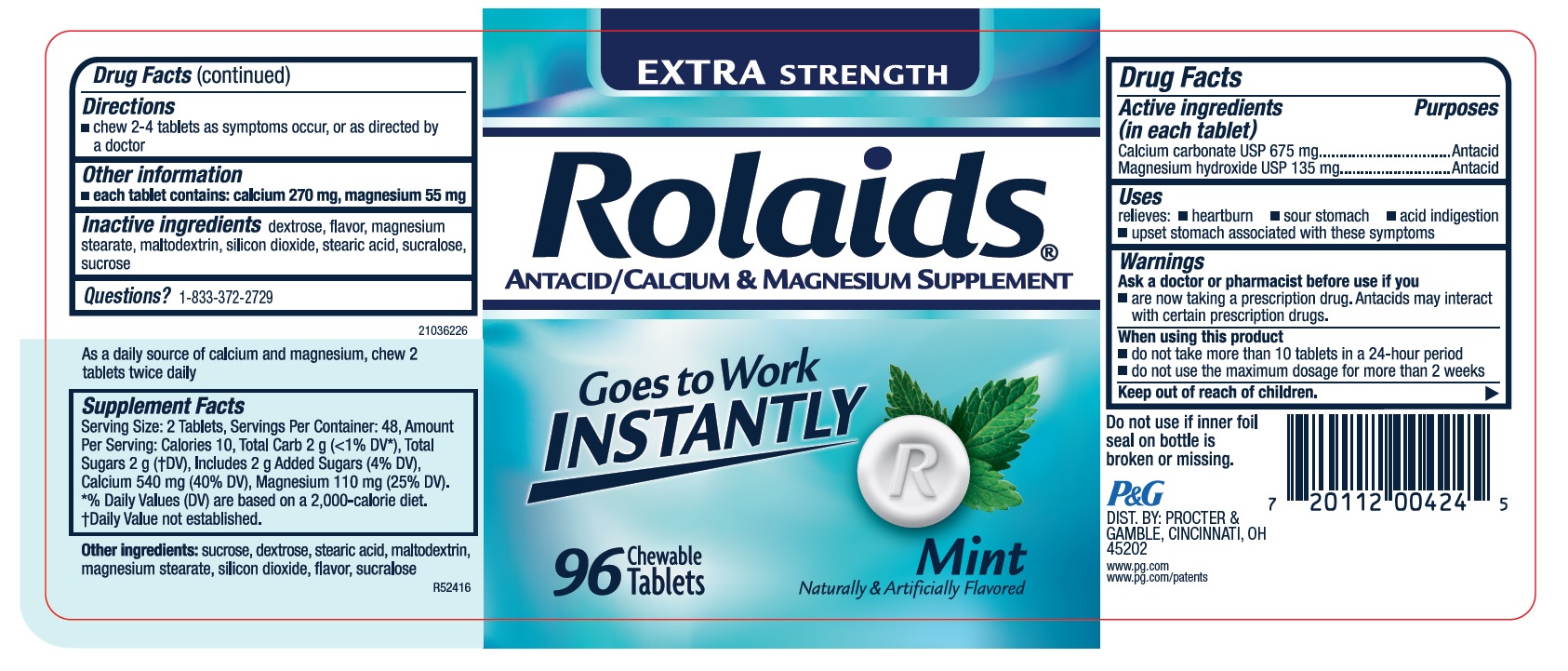 DRUG LABEL: Rolaids Extra Strength Antacid
NDC: 69423-827 | Form: TABLET, CHEWABLE
Manufacturer: THE PROCTER & GAMBLE MANUFACTURING COMPANY
Category: otc | Type: HUMAN OTC DRUG LABEL
Date: 20251003

ACTIVE INGREDIENTS: CALCIUM CARBONATE 675 mg/1 1; MAGNESIUM HYDROXIDE 135 mg/1 1
INACTIVE INGREDIENTS: DEXTROSE; MAGNESIUM STEARATE; SILICON DIOXIDE; STEARIC ACID; SUCRALOSE; SUCROSE; MALTODEXTRIN

Rolaids Extra Strength Tablets Mint

Rolaids Extra Strength Mint

Drug Facts

Active ingredient (in each tablet)

Calcium carbonate USP 675 mg
Magnesium hydroxide USP 135 mg

Purpose

Antacid

Antacid

Uses

relieves:

- heartburn
- sour stomach
- acid indigestion

Warnings

Ask a doctor or pharmacist before use if you

are now taking a prescription drug. Antacids may interact with certain prescription drugs.

When using this product

- do not take more than 10 tablets in a 24-hour period
- do not use the maximum dosage for more than 2 weeks

Directions

- chew 2-4 tablets as symptoms occur, or as directed by a doctor

Other information

each tablet contains: calcium 270 mg, magnesium 55 mg

Inactive ingredients

dextrose, flavor, magnesium stearate, maltodextrin, silicon dioxide, stearic acid, sucralose, sucrose

Tamper Evident

Do not use if inner foil seal on bottle is broken or missing.

DIST. BY: PROCTER &

GAMBLE, CINCINNATI, OH

45202

PRINCIPAL DISPLAY PANEL

EXTRASTRENGTH ANTACID
Rolaids®

ANTACID

GOES TO WORK INSTANTLY

Mint Naturally & Artificially Flavored

96 Chewable Tablets